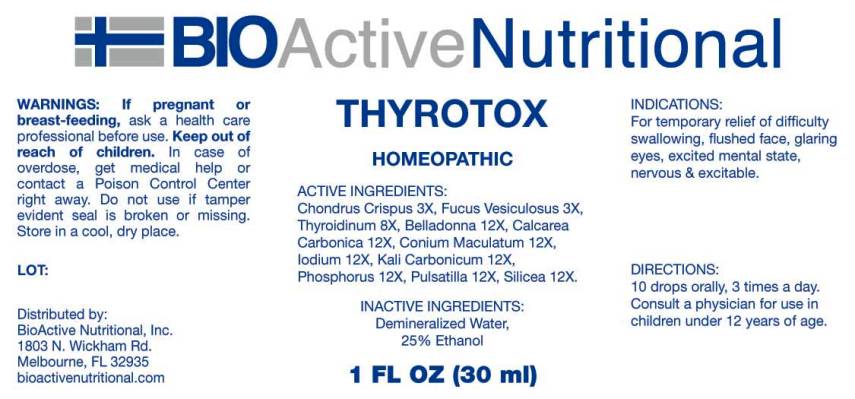 DRUG LABEL: Thyrotox
NDC: 43857-0010 | Form: LIQUID
Manufacturer: BioActive Nutritional, Inc.
Category: homeopathic | Type: HUMAN OTC DRUG LABEL
Date: 20160810

ACTIVE INGREDIENTS: CHONDRUS CRISPUS 3 [hp_X]/1 mL; FUCUS VESICULOSUS 3 [hp_X]/1 mL; SUS SCROFA THYROID 8 [hp_X]/1 mL; ATROPA BELLADONNA 12 [hp_X]/1 mL; OYSTER SHELL CALCIUM CARBONATE, CRUDE 12 [hp_X]/1 mL; CONIUM MACULATUM FLOWERING TOP 12 [hp_X]/1 mL; IODINE 12 [hp_X]/1 mL; POTASSIUM CARBONATE 12 [hp_X]/1 mL; PHOSPHORUS 12 [hp_X]/1 mL; PULSATILLA VULGARIS 12 [hp_X]/1 mL; SILICON DIOXIDE 12 [hp_X]/1 mL
INACTIVE INGREDIENTS: WATER; ALCOHOL

Drug Facts:

ACTIVE INGREDIENTS

Chondrus Crispus 3X, Fucus Vesiculosus 3X, Thyroidinum (Suis) 8X, Belladonna 12X, Calcarea Carbonica 12X, Conium Maculatum 12X, Iodium 12X, Kali Carbonicum 12X, Phosphorus 12X, Pulsatilla 12X, Silicea 12X.

INDICATIONS

For temporary relief of difficulty swallowing, flushed face, glaring eyes, excited mental state, nervous & excitable.

WARNINGS

If pregnant or breast-feeding, ask a health care professional before use.

Keep out of reach of children. In case of overdose, get medical help or contact a Poison Control Center right away.

Do not use if tamper evident seal is broken or missing.

Store in cool, dry place.

DIRECTIONS

10 drops orally, 3 times a day. Consult a physician for use in children under 12 years of age.

INACTIVE INGREDIENTS

Demineralized water, 25% Ethanol.

Keep out of reach of children. In case of overdose, get medical help or contact a Poison Control Center right away.

INDICATIONS:

For temporary relief of difficulty swallowing, flushed face, glaring eyes, excited mental state, nervous & excitable.

QUESTIONS

Distributed by:
BioActive Nutritional, Inc.
1803 N. Wickham Rd.
Melbourne, FL 32935
bioactivenutritional.com

PACKAGE LABEL DISPLAY:

BIOActive Nutritional

THYROTOX

HOMEOPATHIC

1 FL OZ (30 ml)